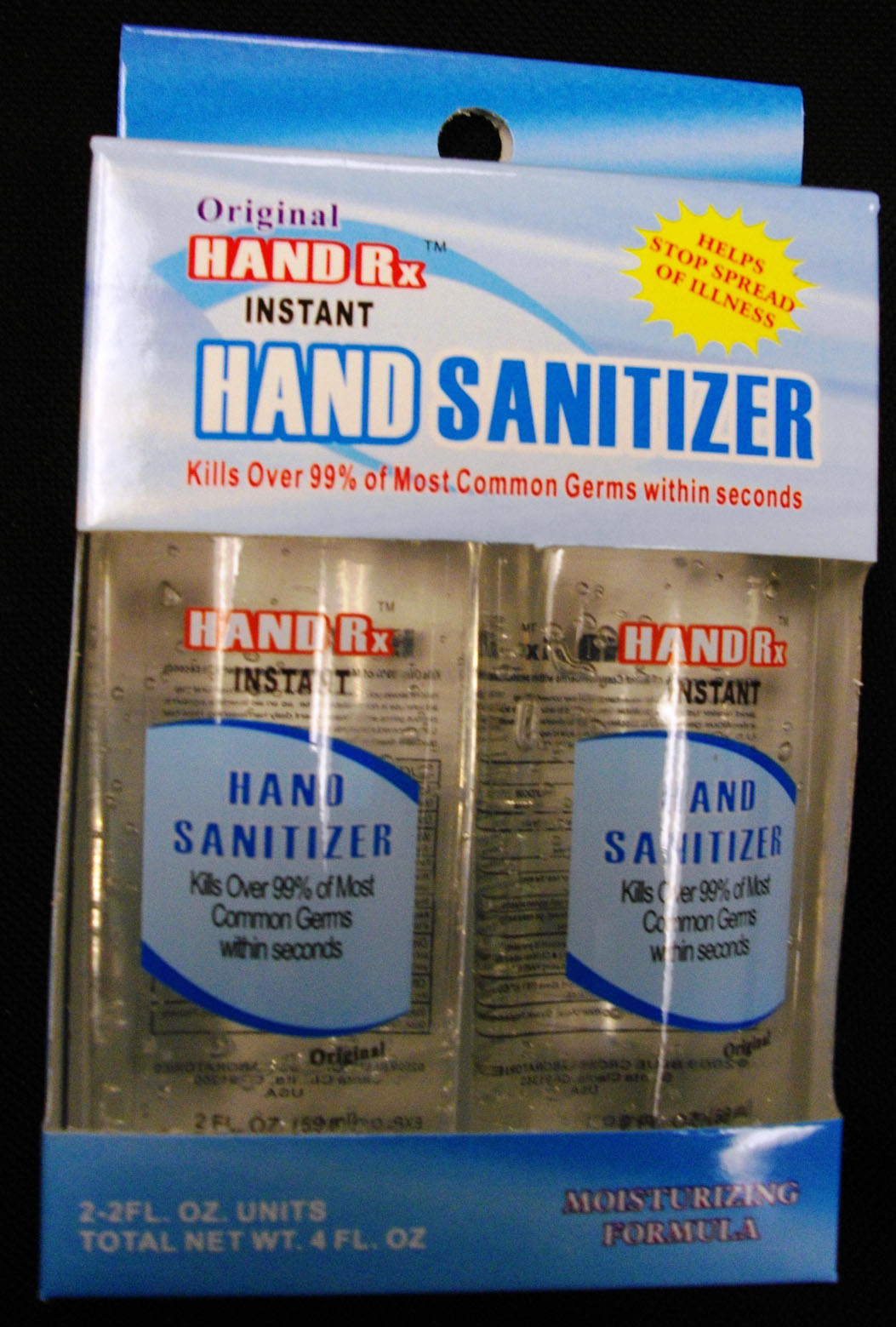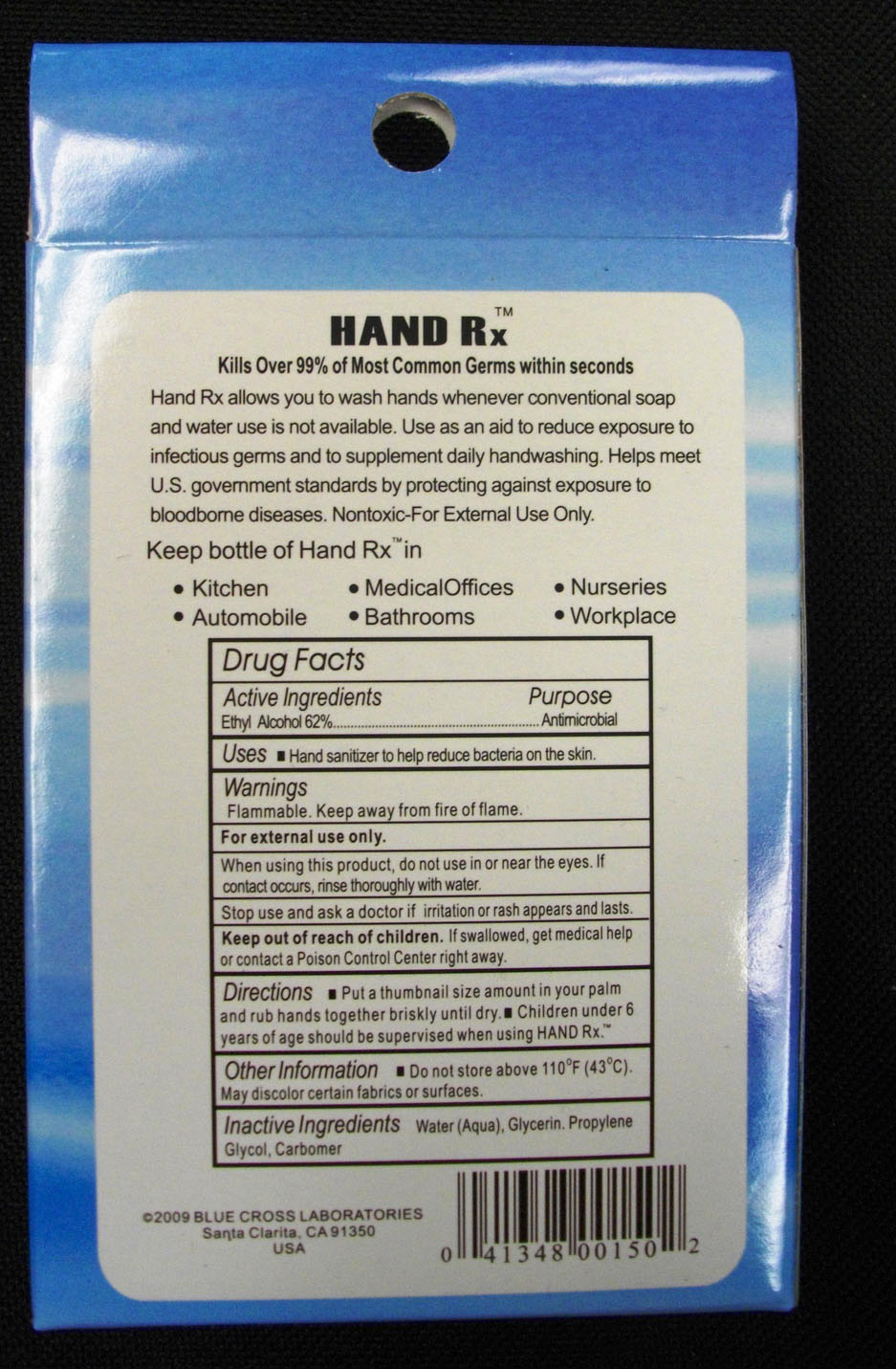 DRUG LABEL: Blue Cross Laboratories
NDC: 22431-111 | Form: LIQUID
Manufacturer: Blue Cross Laboratories
Category: otc | Type: HUMAN OTC DRUG LABEL
Date: 20110308

ACTIVE INGREDIENTS: ALCOHOL 62 mL/100 mL
INACTIVE INGREDIENTS: GLYCERIN; METHOXYISOPROPANOL

Instant Hand Sanitizer

ACTIVE INGREDIENT

PURPOSE

Hand sanitizer to help reduce bacteria on the skin

Keep out of reach of children. If swallowed, get medical help or contact a Poison Control Center right away.

When using this product, do not use in or near the eyes. If contact occurs, rinse thoroughly with water.

WARNINGS

Flammable. Keep away from fire of flame
For external use only
Stop use and ask a doctor if irritation or rash appears and lasts
Do not store above 110o F (43o C)
May discolor certain fabrics on surfaces

DOSAGE AND ADMINISTRATION

put a thumbnail size amount in your palm and rub hands together briskly until dry.
children under 6 years of age should be supervised when using HAND Rx.

INACTIVE INGREDIENT

Water (Aqua), Glycerin, Propylene Glycol, Glycol, Carbomber

PACKAGE LABEL

Hand Rx Instant Hand Sanitizer
2-2FL. OZ. Units
Total Net Wt. 4 FL OZ.